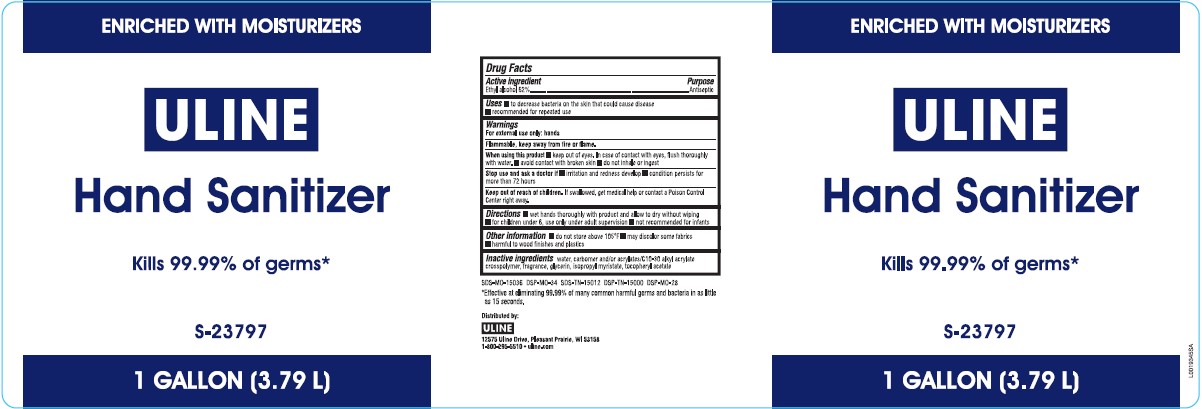 DRUG LABEL: Alcohol
NDC: 69790-849 | Form: LIQUID
Manufacturer: Uline
Category: otc | Type: HUMAN OTC DRUG LABEL
Date: 20260217

ACTIVE INGREDIENTS: ALCOHOL 62 mg/1 mL
INACTIVE INGREDIENTS: WATER; CARBOMER INTERPOLYMER TYPE A (ALLYL SUCROSE CROSSLINKED); GLYCERIN; ISOPROPYL MYRISTATE; TOCOPHEROL

Uline 849.001/849BA
Moisturizing Hand Sanitizer

Active ingredient

Ethyl Alcohol 62%

Purpose

Antiseptic

Uses

- to decrease bacteria on the skin that could cause disease
- recommended for repeated use

Warnings

For exterenal use only: hands

Flammable, keep away from fire or flame.

When using this product

- keep out of eyes. In case of contact with eyes, flush thoroughly with water.
- avoid contact with broken skin
- do not inhale or ingest

Stop use and ask a doctor if

- irritation and redness develop
- condition persists for more than 72 hours

Keep out of reach of children.

If swallowed, get medical help or contact a Poison Control Center right away.

Directions

- wet hands thoroughly with product and allow to dry without wiping
- for children under 6, use only under adult supervision
- not recommended for infants

Other information

- do not store above 105⁰F
- may discolor some fabrics
- harmful to wood finishes and plastics

Inactive ingredients

water, carbomer and/or acrylates/C10-30 alkyl acrylate crosspolymer, fragrance, glycerin, isopropyl myristate, tocopheryl acetate

ADVERSE REACTION

Distributed by: ULINE

12575 Uline Drive, Pleasant Prairie, WI 53158

1-800-295-5510 uline.com

*Effective at eliminating 99.99% of many common harmful germs and bacteria in as little as 15 seconds.

SDS-MO-15036 DSP-MO-34 SDS-TN-15012 DSP-TN-15000 DSP-MO-28

principal display panel

ENRICHED WITH MOISTURIZERS

ULINE

Hand Sanitizer

Kills 99.99% of germs*

S-23797

1 GALLON (3.79 L)